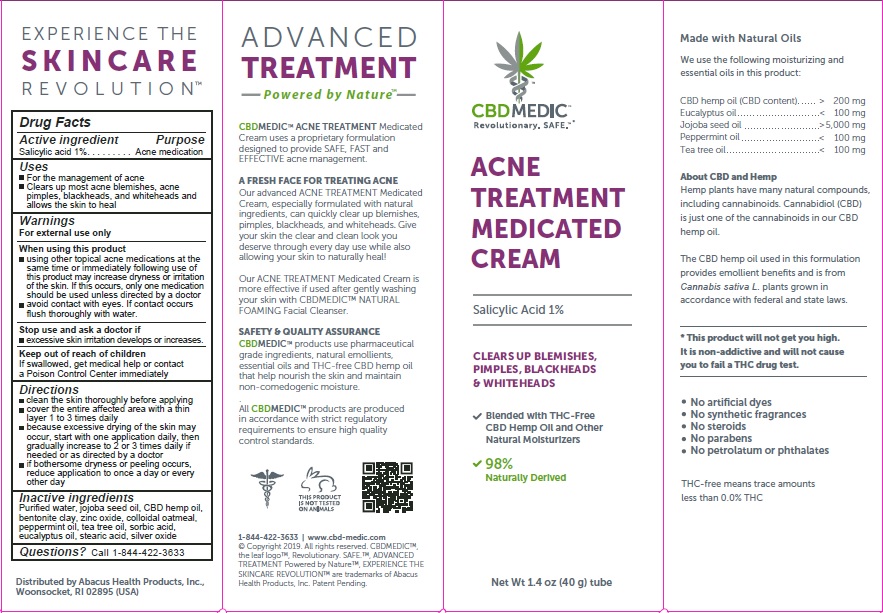 DRUG LABEL: CBDMEDIC Acne Treatment
NDC: 24909-767 | Form: CREAM
Manufacturer: AIDANCE SKINCARE & TOPICAL SOLUTIONS, LLC
Category: otc | Type: HUMAN OTC DRUG LABEL
Date: 20191227

ACTIVE INGREDIENTS: SALICYLIC ACID 10 mg/1 g
INACTIVE INGREDIENTS: BENTONITE; OATMEAL; EUCALYPTUS OIL; HEMP; JOJOBA OIL; PEPPERMINT OIL; WATER; SILVER OXIDE; SORBIC ACID; STEARIC ACID; TEA TREE OIL; ZINC OXIDE

CBDMEDIC Acne Treatment

Active Ingredients and Purpose

Salicylic Acid 1% (Acne Medication)

Uses

• For the management of acne
• Clears up most acne blemishes, acne pimples, blackheads, and whiteheads and allows the skin to heal

Warnings

For external use only
When using this product
• using other topical acne medications at the same time or immediately following use of this product may increase dryness or irritation of the skin. If this occurs, only one medication should be used unless directed by a doctor
• avoid contact with eyes. If contact occurs ﬂush thoroughly with water
Stop use and ask a doctor if
• excessive skin irritation develops or increases
Keep out of reach of children
If swallowed, get medical help or contact a Poison Control Center immediately

Directions:

• clean the skin thoroughly before applying
• cover the entire aﬀected area with a thin layer 1 to 3 times daily
• because excessive drying of the skin may occur, start with one application daily, then gradually increase to 2 or 3 times daily if needed or as directed by a doctor
• if bothersome dryness or peeling occurs, reduce application to once a day or every other day

Inactive ingredients

Purified water, jojoba seed oil, CBD hemp oil, bentonite clay, zinc oxide, colloidal oatmeal, peppermint oil, tea tree oil, sorbic acid, eucalyptus oil, stearic acid, silver oxide

Questions?

Call 1-844-422-3633